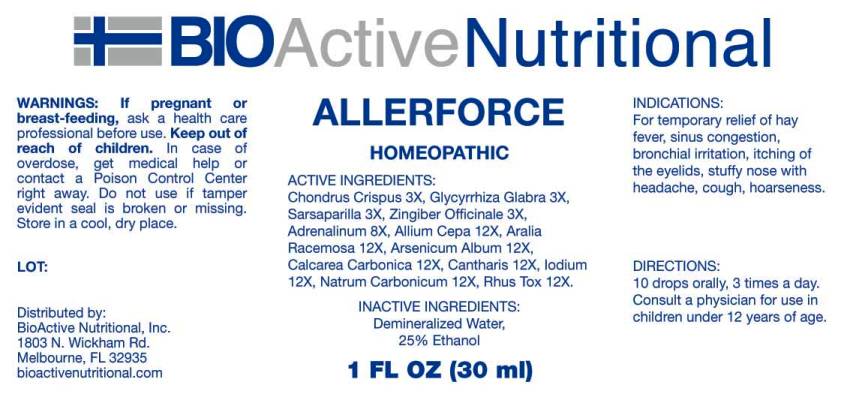 DRUG LABEL: Allerforce
NDC: 43857-0016 | Form: LIQUID
Manufacturer: BioActive Nutritional, Inc.
Category: homeopathic | Type: HUMAN OTC DRUG LABEL
Date: 20230605

ACTIVE INGREDIENTS: CHONDRUS CRISPUS 3 [hp_X]/1 mL; GLYCYRRHIZA GLABRA 3 [hp_X]/1 mL; SMILAX ORNATA ROOT 3 [hp_X]/1 mL; GINGER 3 [hp_X]/1 mL; EPINEPHRINE 8 [hp_X]/1 mL; ONION 12 [hp_X]/1 mL; ARALIA RACEMOSA ROOT 12 [hp_X]/1 mL; ARSENIC TRIOXIDE 12 [hp_X]/1 mL; OYSTER SHELL CALCIUM CARBONATE, CRUDE 12 [hp_X]/1 mL; LYTTA VESICATORIA 12 [hp_X]/1 mL; IODINE 12 [hp_X]/1 mL; SODIUM CARBONATE 12 [hp_X]/1 mL; TOXICODENDRON PUBESCENS LEAF 12 [hp_X]/1 mL
INACTIVE INGREDIENTS: WATER; ALCOHOL

Drug Facts:

ACTIVE INGREDIENTS:

Chondrus Crispus 3X, Glycyrrhiza Glabra 3X, Sarsaparilla 3X, Zingiber Officinale 3X, Adrenalinum 8X, Allium Cepa 12X, Aralia Racemosa 12X, Arsenicum Album 12X, Calcarea Carbonica 12X, Cantharis 12X, Iodium 12X, Natrum Carbonicum 12X, Rhus Tox 12X.

INDICATIONS:

For temporary relief of hay fever, sinus congestion, bronchial irritation, itching of the eyelids, stuffy nose with headache, cough, hoarseness.

WARNINGS:

If pregnant or breast-feeding, ask a health care professional before use.

Keep out of reach of children. In case of overdose, get medical help or contact a Poison Control Center right away.

Do not use if tamper evident seal is broken or missing.

Store in cool, dry place.

DIRECTIONS:

10 drops orally, 3 times a day. Consult a physician for use in children under 12 years of age.

INACTIVE INGREDIENTS:

Demineralized water, 25% Ethanol.

Keep out of reach of children. In case of overdose, get medical help or contact a Poison Control Center right away.

INDICATIONS:

For temporary relief of hay fever, sinus congestion, bronchial irritation, itching of the eyelids, stuffy nose with headache, cough, hoarseness.

QUESTIONS:

Distributed by:
BioActive Nutritional, Inc.
1803 N. Wickham Rd.
Melbourne, FL 32935
bioactivenutritional.com

PACKAGE LABEL DISPLAY:

BIOActive Nutritional

ALLERFORCE

HOMEOPATHIC

1 FL OZ (30 ml)